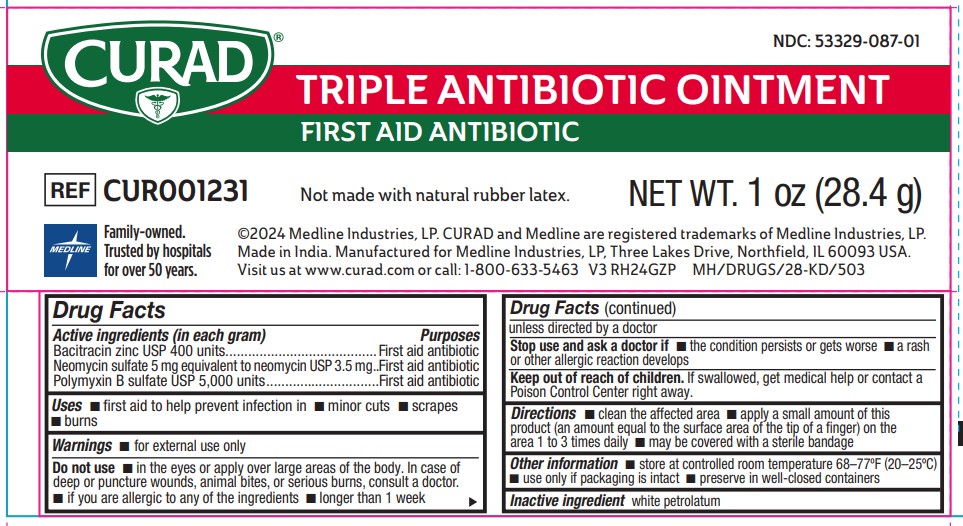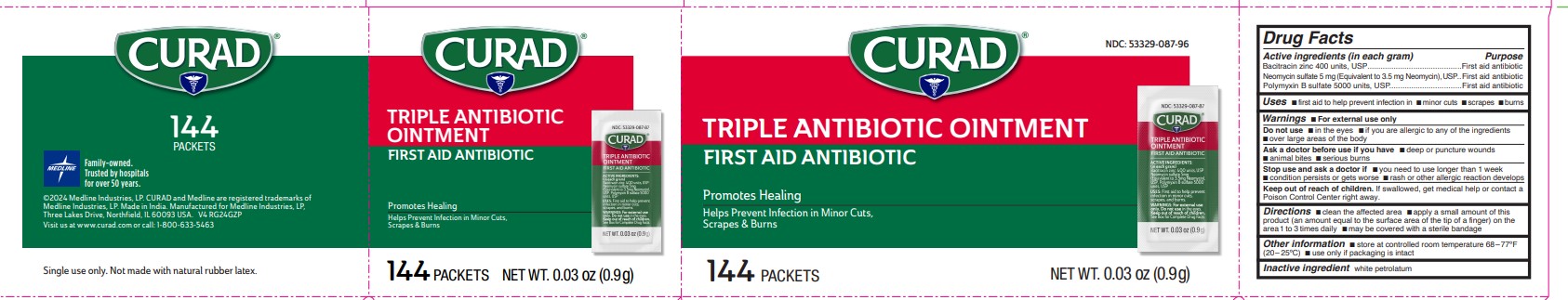 DRUG LABEL: Triple Antibiotic
NDC: 53329-087 | Form: OINTMENT
Manufacturer: Medline Industries, LP
Category: otc | Type: HUMAN OTC DRUG LABEL
Date: 20251009

ACTIVE INGREDIENTS: BACITRACIN ZINC 400 [USP'U]/1 g; NEOMYCIN SULFATE 3.5 mg/1 g; POLYMYXIN B SULFATE 5000 [USP'U]/1 g
INACTIVE INGREDIENTS: WHITE PETROLATUM

087 Curad Triple Antibiotic Ointment

Active ingredient (in each gram)

Bacitracin Zinc 400 units, USP

Neomycin Sulfate 5 mg (Equivalent to 3.5 mg. Neomycin), USP

Polymyxin B Sulfate 5000 units, USP

Purpose

First Aid Antibiotic

First Aid Antibiotic

First Aid Antibiotic

Uses

First aid to help prevent infection in

- minor cuts
- scrapes
- burns

Warnings

For external use only

Do not use

- in the eyes
- if you are allergic to any of the ingredients
- over large areas of the body

Ask a doctor before use if you have

- deep or puncture wounds
- animal bites
- serious burns

Stop use and ask a doctor if

- you need to use longer than 1 week
- condition persists or gets worse
- rash or other allergic reaction develops

Keep out of reach of children.

If swallowed, get medical help or contact a Poison Control Center right away.

Directions

- clean the affected area.
- apply a small amount of this product (an amount equal to the surface area of the tip of a finger) on the area 1 to 3 times daily.
- May be covered with a sterile bandage.

Other information

- Store at controlled room temperature 68-77°F (20°-25°C).
- use only if packaging is intact.

Inactive ingredients

white petrolatum

Manufacturing Information

Made in India.

Manufactured for Medline Industries, LP,

Three Lakes Drive, Northfield, IL 60093 USA

Made in USA of domestic and imported materials.

Visit us at www.curad.com or call: 1-800-633-5463

REF: CUR001209

RECENT MAJOR CHANGES

- Warnings and Precautions